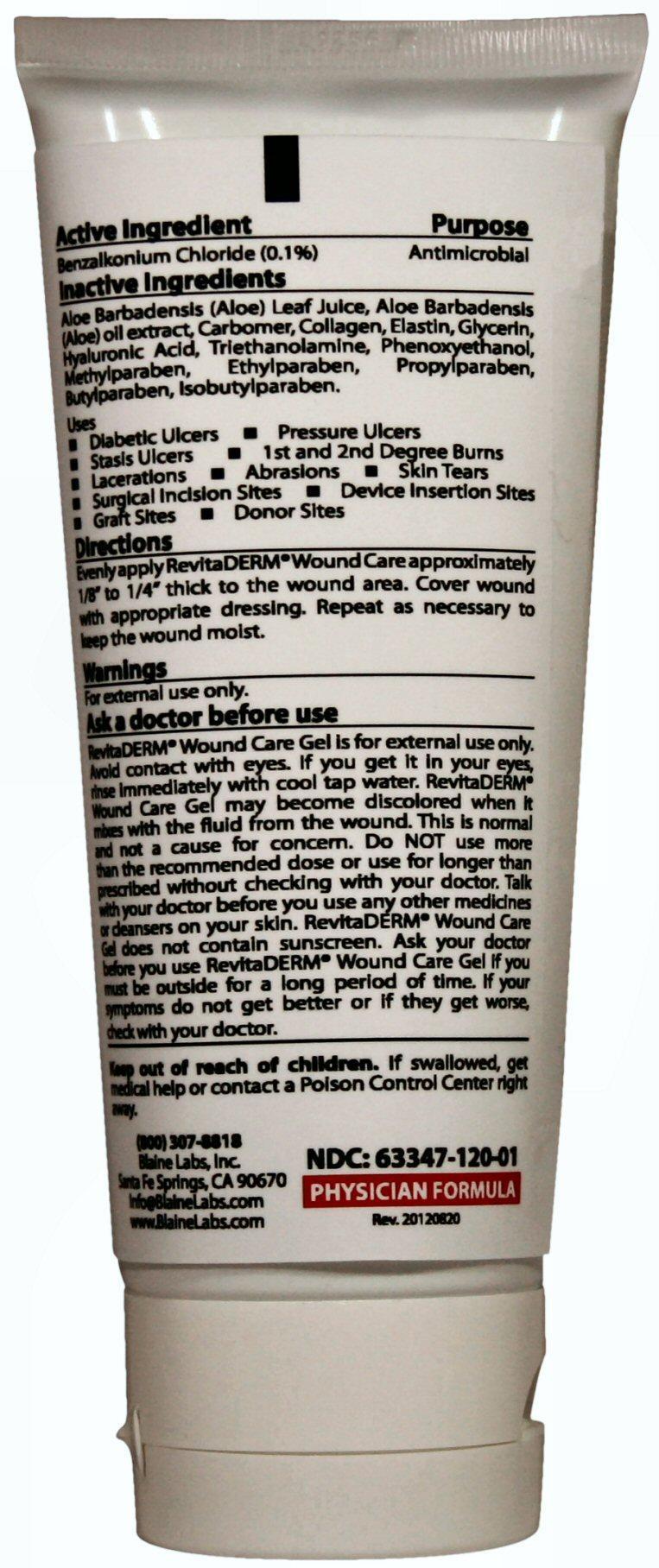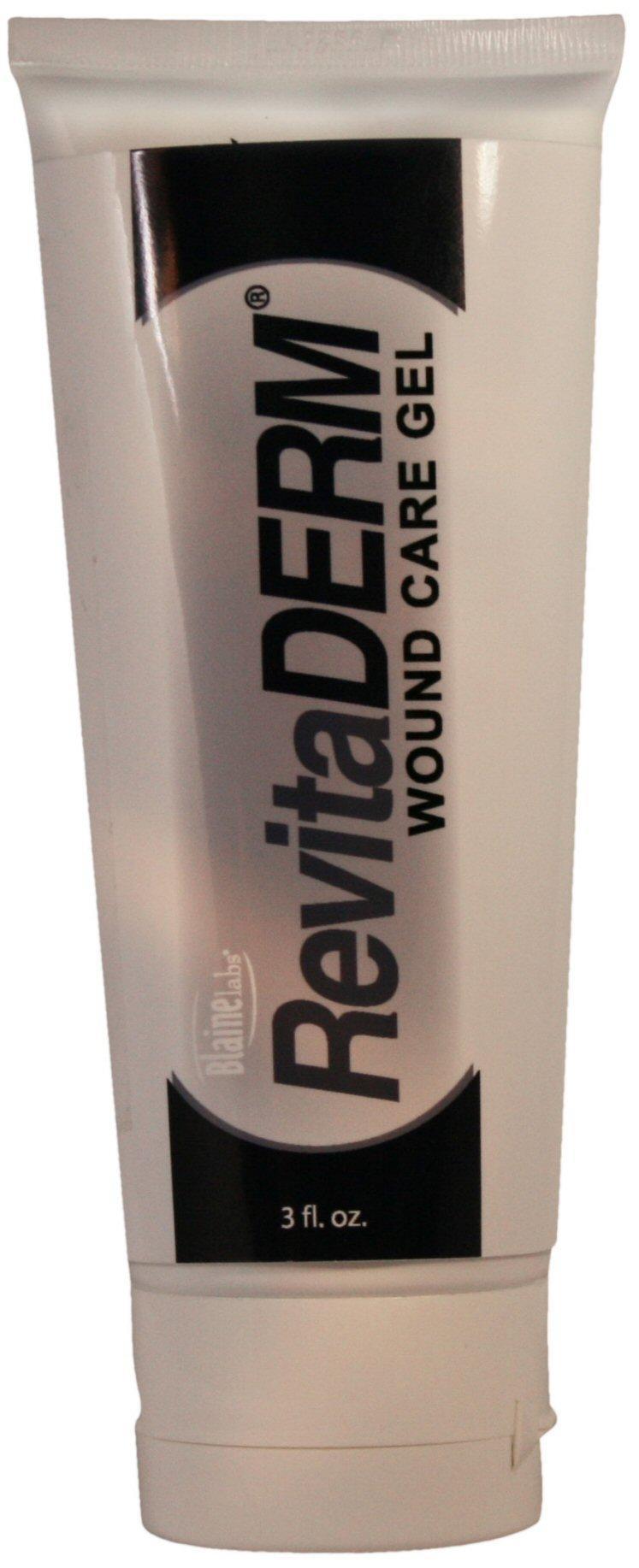 DRUG LABEL: RevitaDERM Wound Care
                
NDC: 63347-120 | Form: GEL
Manufacturer: Blaine Labs Inc.
Category: otc | Type: HUMAN OTC DRUG LABEL
Date: 20231221

ACTIVE INGREDIENTS: BENZALKONIUM CHLORIDE 170 mg/89 mL
INACTIVE INGREDIENTS: ALOE VERA LEAF; CARBOMER INTERPOLYMER TYPE A (ALLYL SUCROSE CROSSLINKED); HYDROLYZED ELASTIN, BOVINE, ALKALINE (1000 MW); GLYCERIN; HYALURONIC ACID; TROLAMINE; PHENOXYETHANOL; METHYLPARABEN; ETHYLPARABEN; PROPYLPARABEN; BUTYLPARABEN; ISOBUTYLPARABEN

Active Ingredients

Benzalkonium Chloride (0.1%)

Purpose

Antimicrobial

Keep out of reach of children. If swallowed, get medical help or contact a Poison Control Center right away.

Uses

* 1st and 2nd Degree Burns
* Stasis Ulcers
* Pressure Ulcers
* Diabetic Ulcers
* Lacerations
* Abrasions
* Skin Tears
* Surgical Incision Sites
* Device Insertion Sites
* Graft Sites
* Donor Sites

Warnings

For external use only.

Ask a doctor before use

RevitaDERM Wound Care Gel is for external use only. Avoid contact with eyes. If you get it in your eyes, rinse immediately with cool tap water. RevitaDERM Wound Care Gel may become discolored when it mixes with fluid from the wound. This is normal and not a cause for concern. Do NOT use more than the recommended dose or use for longer than prescribed without checking with your doctor. Talk with your doctor before you use any other medicines or cleansers on your skin. RevitaDERM Wound Care Gel does not contain sunscreen. Ask you doctor before you use RevitaDERM Wound Care Gel if you must be outside for a long period of time. If your symptoms do not get better or if they get worse, check with your doctor.

Directions

Evenly apply RevitaDERM Wound Care approximately 1/8 inch to 1/4 inch thick to the wound area. Cover wound with appropriate dressing. Repeat as necessary to keep the wound moist.

Inactive Ingredients

Aloe Barbadensis (Aloe) Leaf Juice, Aloe Barbadensis (Aloe) oil extract, Carbomer, Collagen, Elastin, Glycerin, Hyaluronic Acid, Triethanolamine, Phenoxyethanol, Methylparaben, Ethylparaben, Propylparaben, Butylparaben, Isobutylparaben.

Product Label

Blaine Labs
RevitaDERM WOUND CARE GEL
3 fl. oz. PHYSICIAN FORMULA
NDC: 63347-120-01
(800) 307-8818 Info@BlaineLabs.com www.BlaineLabs.com Blaine Labs, Inc. Santa Fe Springs, CA 90670 Rev. 20120820

res